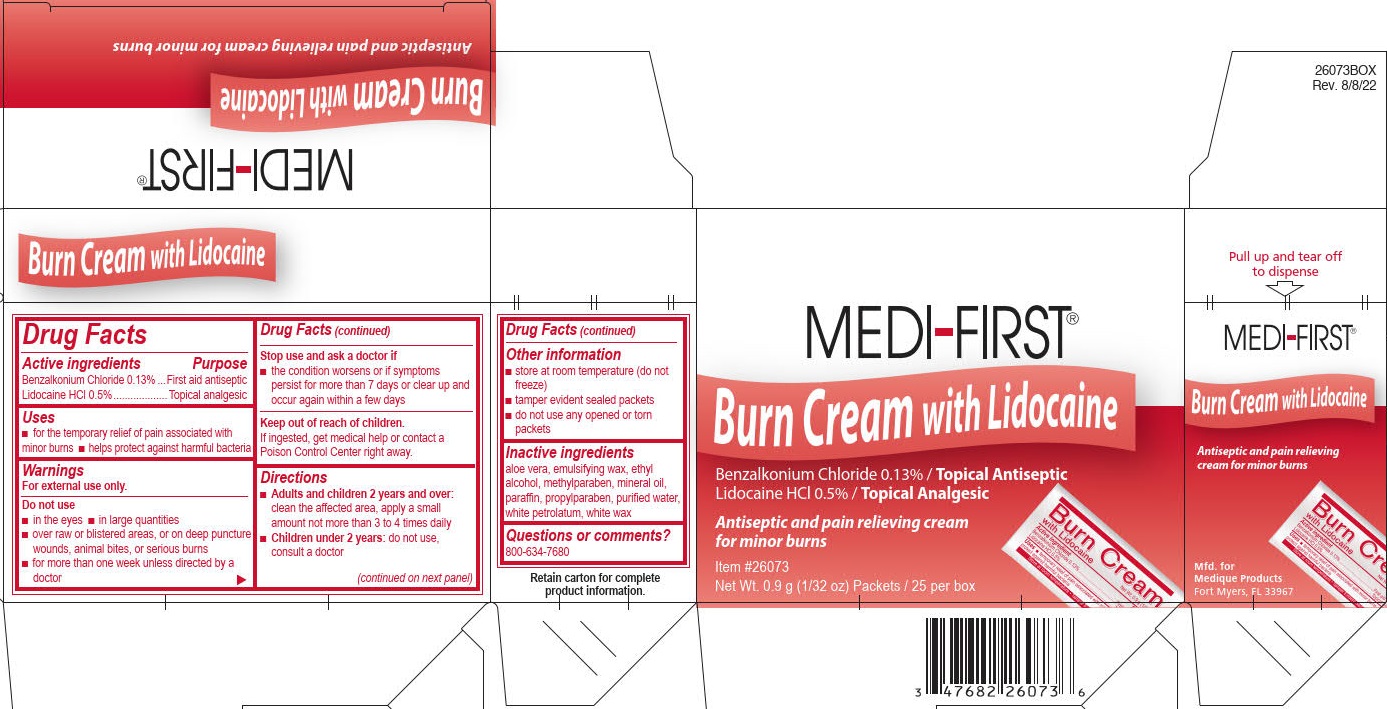 DRUG LABEL: Burn with Lidocaine
NDC: 47682-260 | Form: CREAM
Manufacturer: Unifirst First Aid Corporation
Category: otc | Type: HUMAN OTC DRUG LABEL
Date: 20250908

ACTIVE INGREDIENTS: BENZALKONIUM CHLORIDE 1.3 mg/1 g; LIDOCAINE HYDROCHLORIDE 5 mg/1 g
INACTIVE INGREDIENTS: MINERAL OIL; ALCOHOL; METHYLPARABEN; ALOE VERA LEAF; PARAFFIN; PETROLATUM; PROPYLPARABEN; WATER; WHITE WAX

Medi-First Burn Cream with Lidocaine

Drug Facts

Active ingredients

Benzalkonium Chloride 0.13%

Lidocaine HCl 0.5%

Purpose

First aid antiseptic

Topicall analgesic

Uses

- for the temporary releif of pain associated with minor burns
- helps protect against harmful bacteria

Warnings

For external use only.

Do not use

- in the eyes
- in large quantities
- over raw surfaces or blistered areas, or on deep puncture wounds, animal bites, or serious burns
- for more than 1 week unless directed by a doctor

Stop use and ask doctor if

- the condition worsens or if symptoms persists for more than 7 days or clear up andoccur again within a few days

Keep out of reach of children.

If ingested, get medical help or contact a Poison Control Center right away.

Directions

Adults and children 2 years and over:

- clean the affected area, apply a small amount not more than 3 to 4 times daily

Children under 12 years:

- do not use, consult a doctor

Other information

- store at room temperature (do not freeze)
- tamper evident sealed packets
- do not use any opened or torn packets

Inactive ingredients

aloe vera, emulsifying wax, ethyl alcohol, methylparaben, mineral oil, paraffin, propylparaben, purified water, white petrolatum, white wax

Questions or comments? 1-800-634-7680

MF Burn Cream with Lidocaine Label

MEDI-FIRST®

BURN CREAM with Lidocaine

Benzalkonium Chloride 0.13% / Topical Antiseptic

Lidocaine HCl 0.5% / Topical Analgesic

Antiseptic and pain relieving cream for minor cuts, scrapes and burns

Product # 26073

0.9 gram Packets - 25 per box